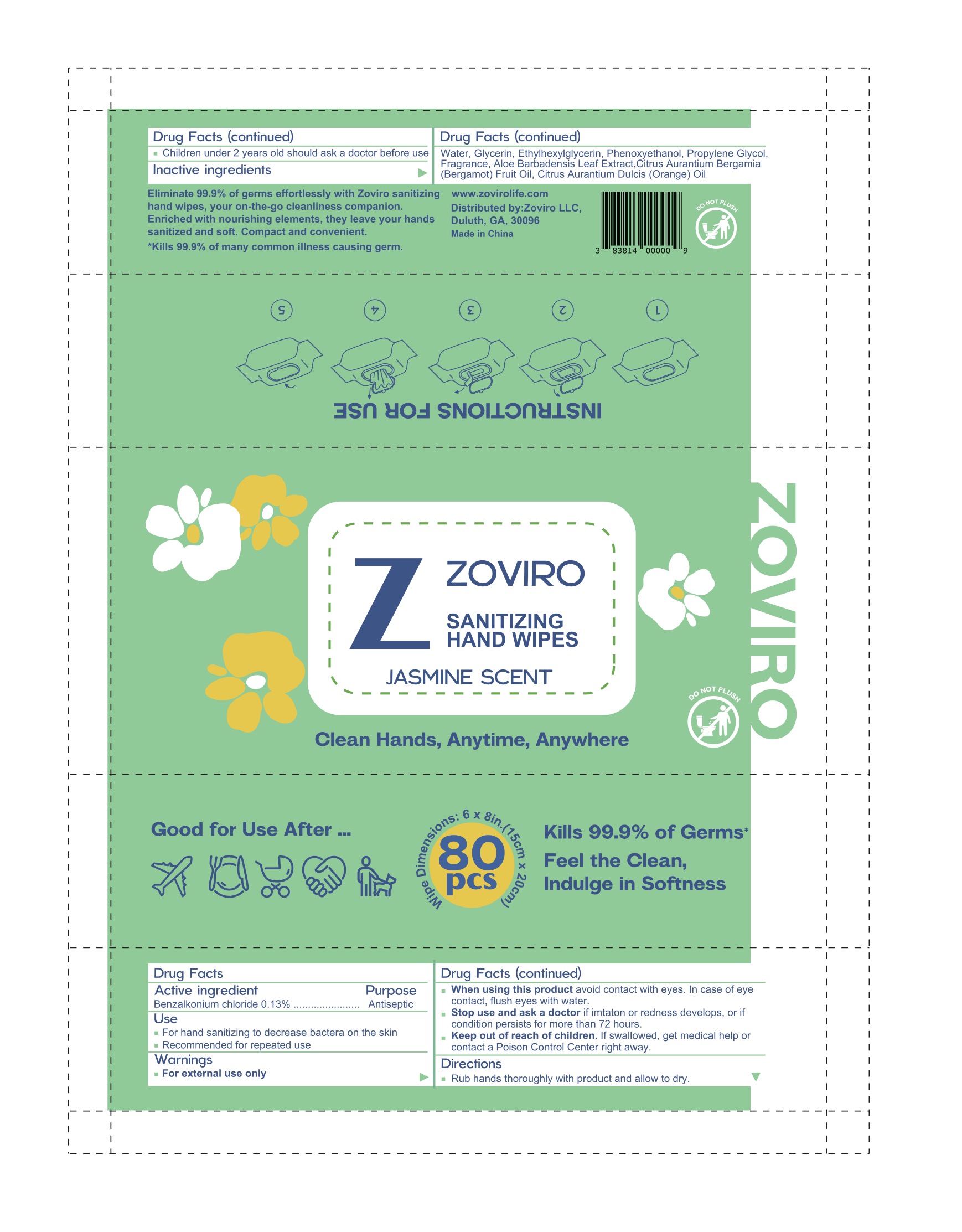 DRUG LABEL: Zoviro
NDC: 83814-003 | Form: SWAB
Manufacturer: Zoviro, LLC
Category: otc | Type: HUMAN OTC DRUG LABEL
Date: 20250326

ACTIVE INGREDIENTS: BENZALKONIUM CHLORIDE 0.13 g/100 g
INACTIVE INGREDIENTS: ETHYLHEXYLGLYCERIN; GLYCERIN; ALOE VERA LEAF; PHENOXYETHANOL; WATER; BERGAMOT OIL; ORANGE OIL; PROPYLENE GLYCOL

Zoviro Alcohol-Free Hand Sanitizing Wipes Jasmine

Active ingredient

Benzalkonium chloride 0.13%

Purpose

Antiseptic

When using this product avoid contact with eyes. In case of eye contact, flush eyes with water.

Stop use and ask a doctor if imtaton or redness develops, or if condition persists for more than 72 hours.

Keep out of reach of children. If swallowed, get medical help or contact a Poison Control Center right away.

Inactive ingredients

Water, Glycerin, Ethylhexylglycerin, Phenoxyethanol, Propylene Glycol, Fragrance, Aloe Barbadensis Leaf Extract,Citrus Aurantium Bergamia (Bergamot) Fruit Oil, Citrus Aurantium Dulcis (Orange) Oil

Directions

Rub hands thoroughly with product and allow to dry.

Children under 2 years old should ask a doctor before use

Use

For hand sanitizing to decrease bactera on the skin

Recommended for repeated use

Warnings

For external use only